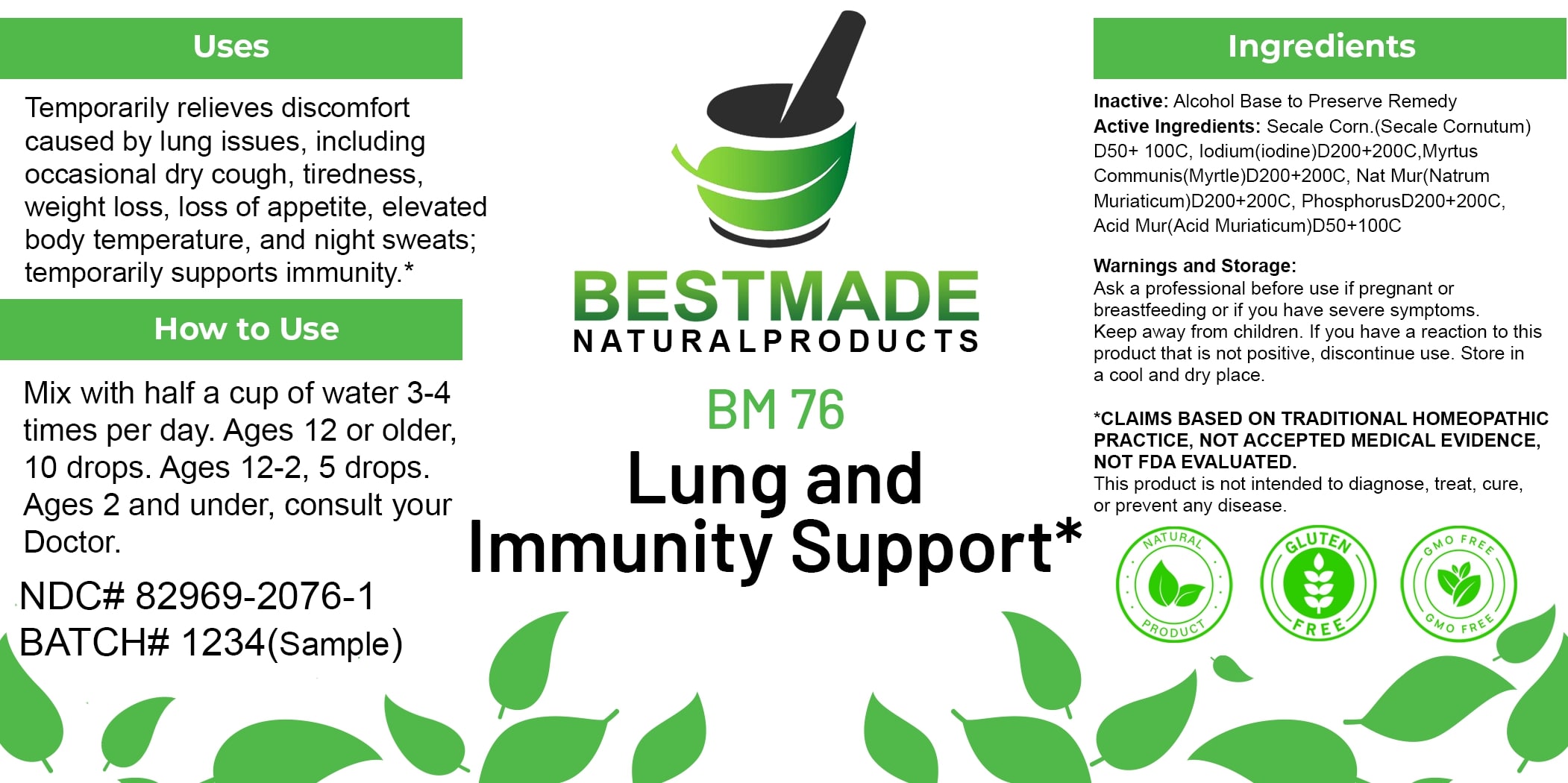 DRUG LABEL: Bestmade Natural Products BM76
NDC: 82969-2076 | Form: LIQUID
Manufacturer: Bestmade Natural Products
Category: homeopathic | Type: HUMAN OTC DRUG LABEL
Date: 20250130

ACTIVE INGREDIENTS: IODINE 200 [hp_C]/200 [hp_C]; MYRTUS COMMUNIS TOP 200 [hp_C]/200 [hp_C]; CLAVICEPS PURPUREA SCLEROTIUM 200 [hp_C]/200 [hp_C]; SODIUM CHLORIDE 200 [hp_C]/200 [hp_C]; HYDROCHLORIC ACID 200 [hp_C]/200 [hp_C]; PHOSPHORUS 200 [hp_C]/200 [hp_C]
INACTIVE INGREDIENTS: ALCOHOL 200 [hp_C]/200 [hp_C]

BM76

DOSAGE AND ADMINISTRATION

How to Use

Mix with half a cup of water 3-4 times per day. Ages 12 or older, 10 drops. Ages 12-2, 5 drops. Ages 2 and under, consult your Doctor.

INACTIVE INGREDIENT

Ingredients

Inactive: Alcohol Base to Preserve Remedy

ACTIVE INGREDIENT

Active Ingredients: Secale Corn (Secale Cornutum) D50+100C, Iodine(iodine)D200+200C, Myrtus Communis(Myrtle)D200+200C, Nat Mur(Natrum Muriaticum)D200+200C, PhosphorusD200+200C, Acid Mur(Acid Muriaticum)D50+100C

Uses

Temporarily relieves discomfort caused by lung issues, including occasional dry cough, tiredness, weight loss, loss of appetite, elevated body temperature, and night sweats; temporarily supports immunity.*

*CLAIMS BASED ON TRADITIONAL HOMEOPATHIC PRACTICE, NOT ACCEPTED MEDICAL EVIDENCE, NOT FDA EVALUATED.

This product is not intended to diagnose, treat, cure, or prevent any disease.

Uses

Temporarily relieves discomfort caused by lung issues, including occasional dry cough, tiredness, weight loss, loss of appetite, elevated body temperature, and night sweats; temporarily supports immunity.*

*CLAIMS BASED ON TRADITIONAL HOMEOPATHIC PRACTICE, NOT ACCEPTED MEDICAL EVIDENCE, NOT FDA EVALUATED.

This product is not intended to diagnose, treat, cure, or prevent any disease.

KEEP OUT OF REACH OF CHILDREN

Warnings and Storage:

Ask a professional before use if pregnant or breastfeeding or if you have severe symptoms. Keep away from children. If you have a reaction to this product that is not positive, discontinue use. Store in a cool and dry place.

Warnings and Storage:

Ask a professional before use if pregnant or breastfeeding or if you have severe symptoms. Keep away from children. If you have a reaction to this product that is not positive, discontinue use. Store in a cool and dry place.

*CLAIMS BASED ON TRADITIONAL HOMEOPATHIC PRACTICE, NOT ACCEPTED MEDICAL EVIDENCE, NOT FDA EVALUATED.

This product is not intended to diagnose, treat, cure, or prevent any disease.

Entire package label